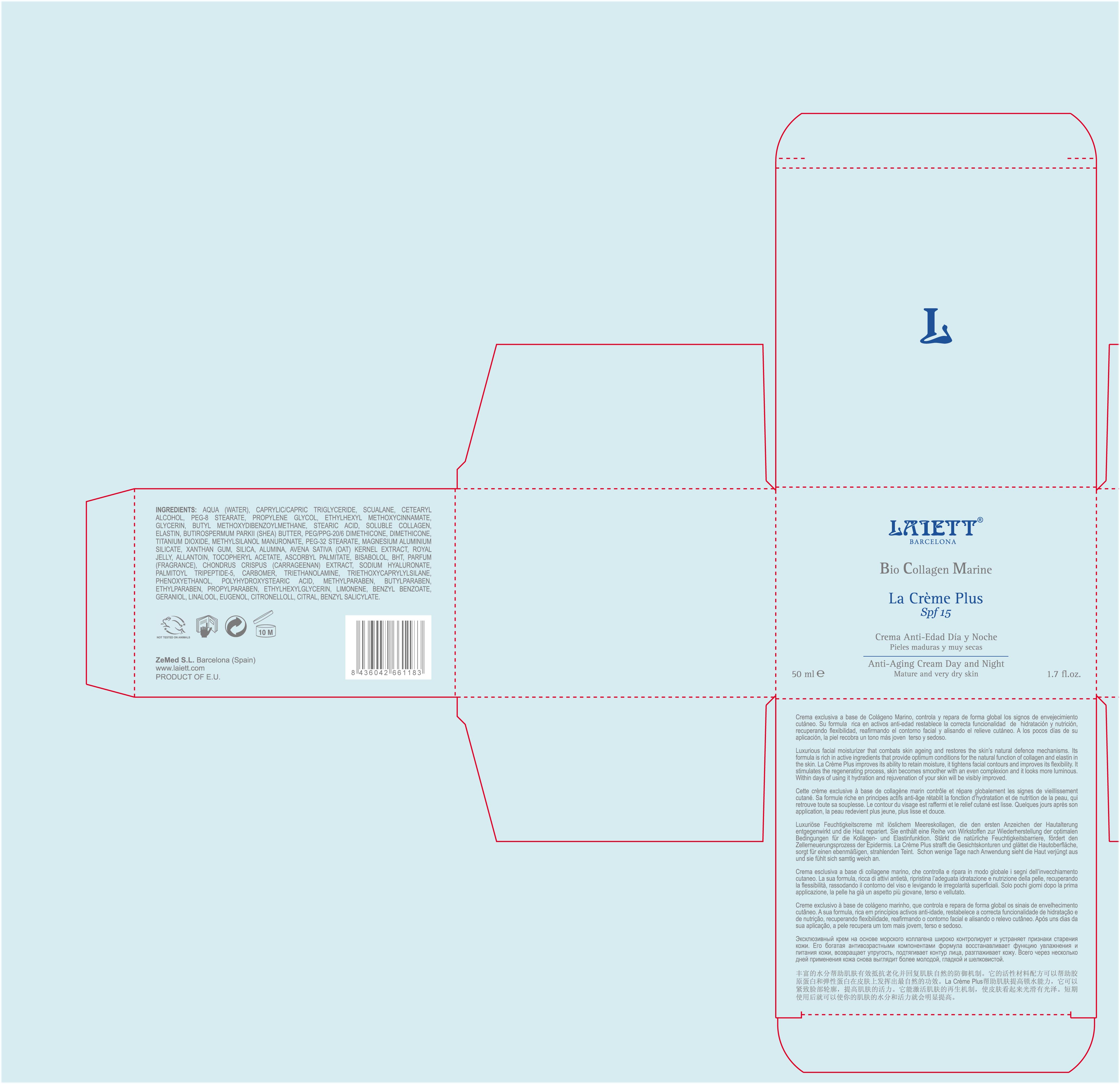 DRUG LABEL: La Creme
NDC: 42248-133 | Form: CREAM
Manufacturer: Zenith Medicosm SL
Category: otc | Type: HUMAN OTC DRUG LABEL
Date: 20120523

ACTIVE INGREDIENTS: OCTINOXATE 3.75 mL/50 mL; AVOBENZONE 1.5 mL/50 mL; TITANIUM DIOXIDE 12.5 mL/50 mL
INACTIVE INGREDIENTS: MAGNESIUM ALUMINUM SILICATE; PROPYLPARABEN; ALPHA-TOCOPHEROL ACETATE; DIMETHICONE; XANTHAN GUM; SHEA BUTTER; WATER; ISOPROPYL PALMITATE; TRICAPRYLIN; PEG-8 STEARATE; SILICON DIOXIDE; PROPYLENE GLYCOL; CHONDRUS CRISPUS; BUTYLATED HYDROXYTOLUENE; ASCORBYL PALMITATE; CARBOMER 934; ROYAL JELLY; AVENA SATIVA FLOWERING TOP; METHYLPARABEN; COLLAGEN, SOLUBLE, FISH SKIN; PALMITOYL TRIPEPTIDE-5; TROLAMINE; CETOSTEARYL ALCOHOL; STEARIC ACID; LEVOMENOL; ALLANTOIN; BUTYLPARABEN; PEG-32 STEARATE; ETHYLPARABEN; GLYCERIN; SQUALENE; BENZYL BENZOATE; HYALURONATE SODIUM; .BETA.-CITRONELLOL, (R)-; LIMONENE, (+/-)-; TRIETHOXYCAPRYLYLSILANE; CITRAL; PHENOXYETHANOL; GERANIOL; POLYHYDROXYSTEARIC ACID (2300 MW); LINALOOL, (+/-)-; EUGENOL; BENZYL SALICYLATE

Drug Facts

Active Ingredient

Octinoxate 7.5%

Avobenzone 3%

Titanium Dioxide 25%

Description

Luxurious facial moisturizer that combats skin ageing and ensures that skin is well nourished and moisturized round-the clock. Its formula is rich in active ingredients that help provide optimum conditions for the natural function of collagen and elastin in the skin. La Creme helps reduce expression lines and wrinkles and improves the skin's flexibility and elasticity. Skin looks firmer and more luminous. Within days of using it there will be a visible improvement.

50ml. 1.7fl. oz.